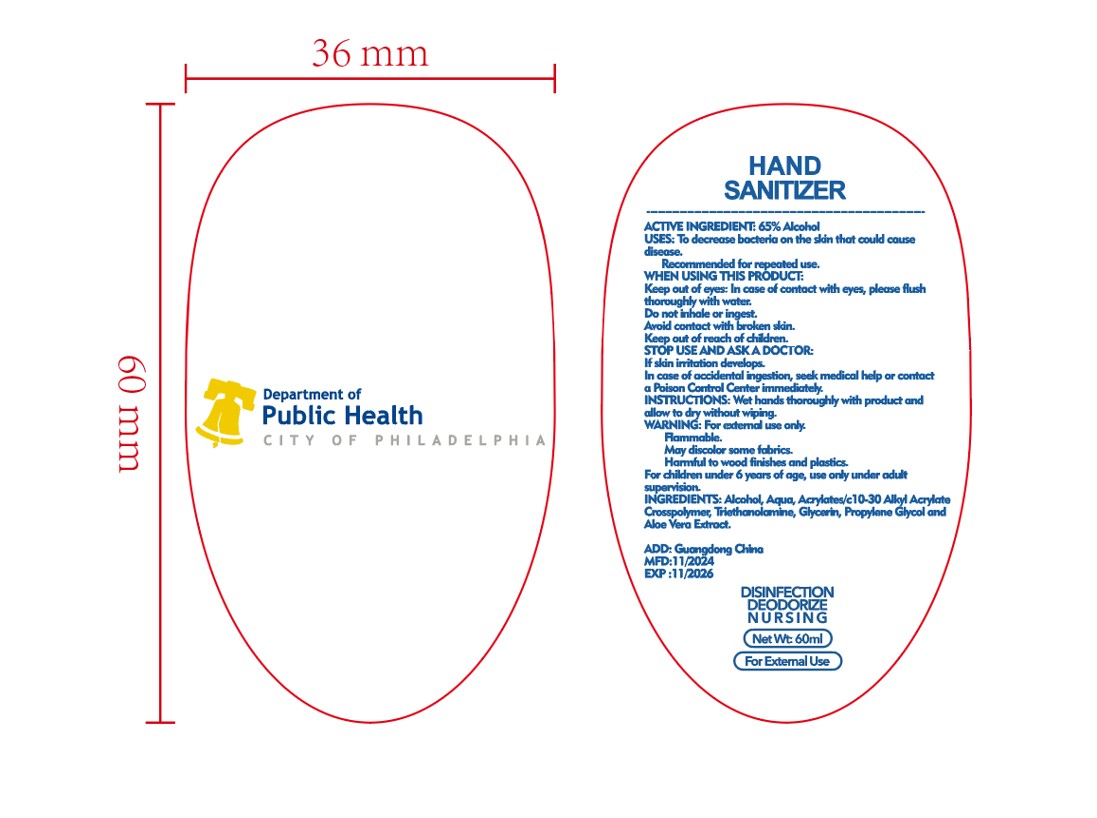 DRUG LABEL: Water-free hand sanitizer
NDC: 85062-001 | Form: LIQUID
Manufacturer: Dongguan Chumei Rubber & Plastic Products Co., Ltd
Category: otc | Type: HUMAN OTC DRUG LABEL
Date: 20241220

ACTIVE INGREDIENTS: ALCOHOL 65 g/100 mL
INACTIVE INGREDIENTS: PROPYLENE GLYCOL; WATER; TRIETHANOLAMINE; POLYACRYLIC ACID (250000 MW); GLYCERIN

Water-free hand sanitizer

ACTIVE INGREDIENT

Alcohol 65%

PURPOSE

Sterilization

KEEP OUT OF REACH OF CHILDREN

Keep out of eyes: ln case of contact with eyes, please fush thoroughly with water.

INDICATIONS AND USAGE

USES: To decrease boeteria on the skin that could cause disease.

WARNINGS

For ecternal use only.

DOSAGE AND ADMINISTRATION

INSIRUCTIONS: Wet hands tharoughly with produet and allow to dry without wiping

INACTIVE INGREDIENT

water
glycerol
Propylene glycol
Polyacrylic
Triethanolamine